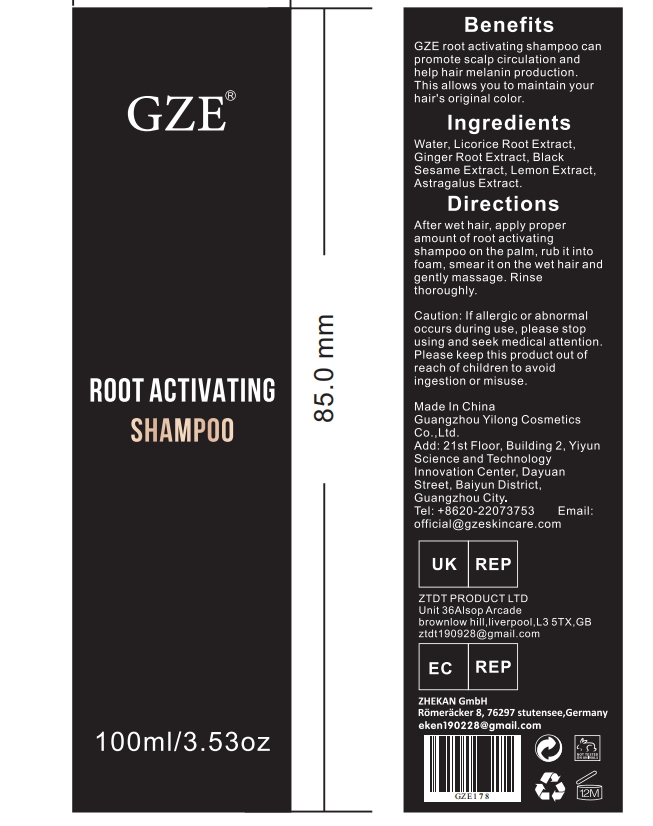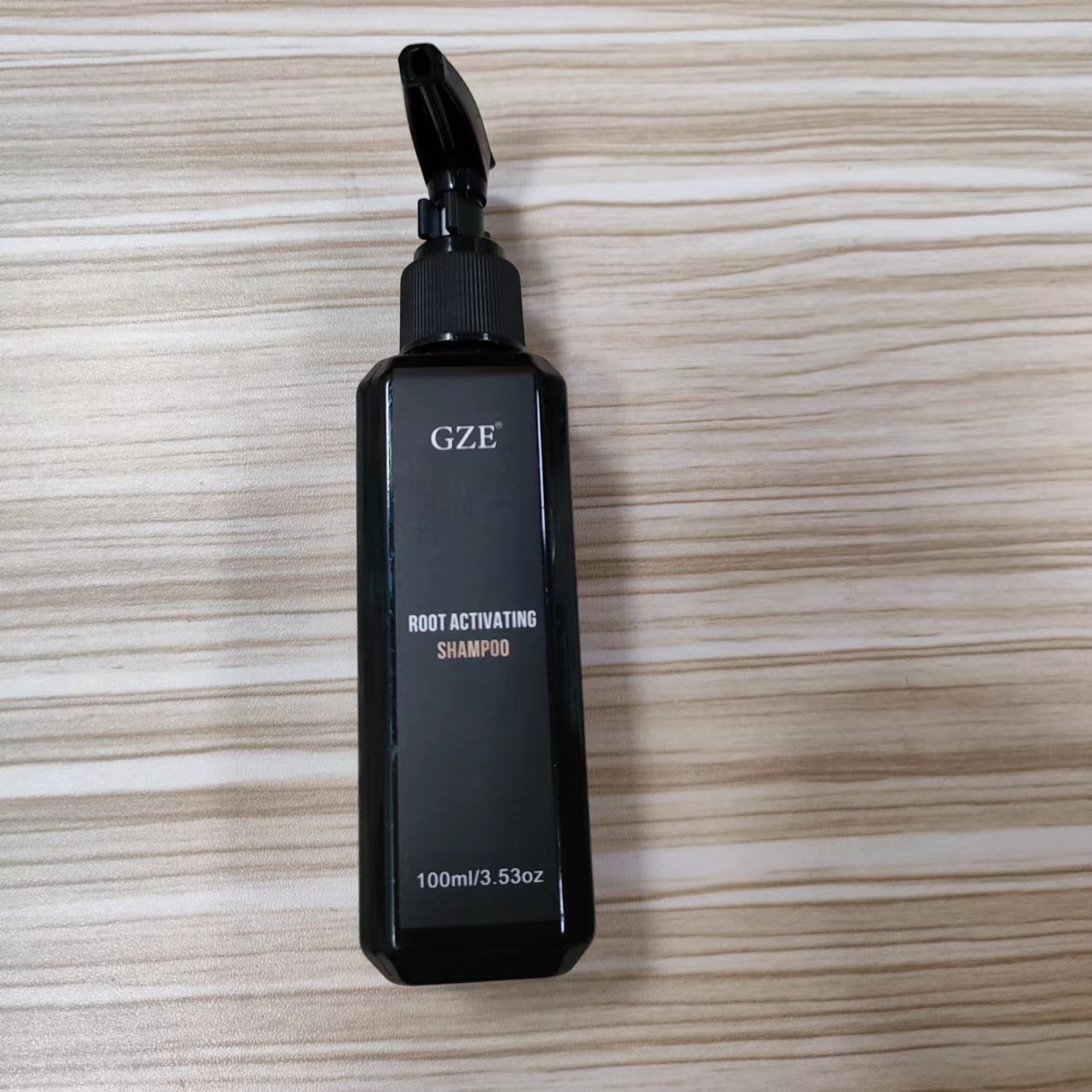 DRUG LABEL: GZE Root ActivatingShampoo
NDC: 83566-178 | Form: SHAMPOO
Manufacturer: Guangzhou Yilong Cosmetics Co., Ltd
Category: otc | Type: HUMAN OTC DRUG LABEL
Date: 20240708

ACTIVE INGREDIENTS: SESAMUM INDICUM WHOLE 10 g/100 mL; ZINGIBER OFFICINALE WHOLE 10 g/100 mL
INACTIVE INGREDIENTS: GLYCYRRHIZA GLABRA WHOLE; ASTRAGALUS MELILOTOIDES WHOLE; WATER; CITRUS LIMON WHOLE

GZE Root Activating Shampoo

ACTIVE INGREDIENT

SESAMUM INDICUM WHOLE
ZINGIBER OFFICINALE WHOLE

PURPOSE

GZE root activating shampoo can promote scalp circulation and help hair melanin production.

INDICATIONS AND USAGE

After wet hair, apply proper amount of root activating shampoo on the palm, rub it into foam,smear it on the wet hair and gently massage.Rinse thoroughly.

WARNINGS

For external use only.

Stop use and ask a doctor if rash occurs.

Do not use on damaged or broken skin.

When using this product keep out of eyes. Rinse with water to remove.

Keep out of reach of children. If swallowed, get medical help or contact a Poison Control Center right away.

DOSAGE AND ADMINISTRATION

After wet hair, apply proper amount of root activating shampoo on the palm, rub it into foam,smear it on the wet hair and gently massage.Rinse thoroughly.

INACTIVE INGREDIENT

Water